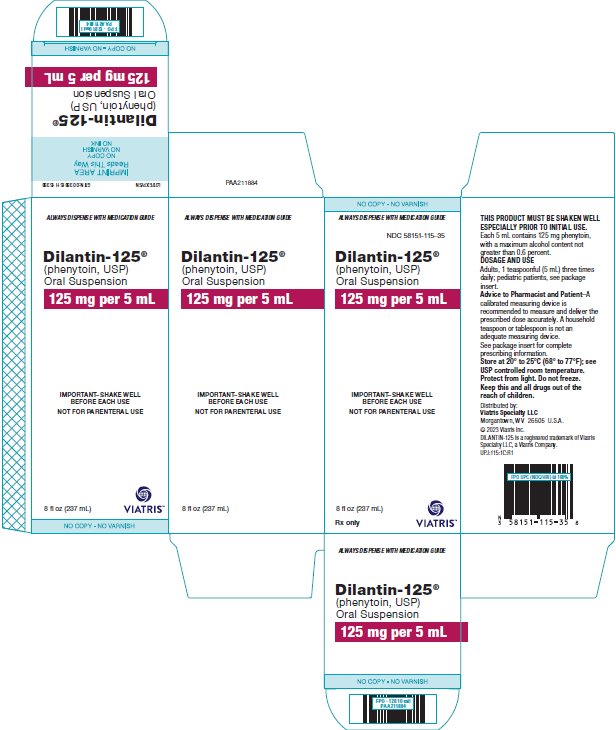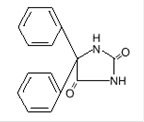 DRUG LABEL: Dilantin-125
NDC: 58151-115 | Form: SUSPENSION
Manufacturer: Viatris Specialty LLC
Category: prescription | Type: HUMAN PRESCRIPTION DRUG LABEL
Date: 20230202

ACTIVE INGREDIENTS: PHENYTOIN 125 mg/5 mL
INACTIVE INGREDIENTS: ALCOHOL; CARBOXYMETHYLCELLULOSE SODIUM, UNSPECIFIED FORM; ANHYDROUS CITRIC ACID; GLYCERIN; MAGNESIUM ALUMINUM SILICATE; POLYSORBATE 40; WATER; SODIUM BENZOATE; SUCROSE; VANILLIN; FD&C YELLOW NO. 6

HIGHLIGHTS OF PRESCRIBING INFORMATION

These highlights do not include all the information needed to use DILANTIN-125® safely and effectively. See full prescribing information for DILANTIN-125®.
DILANTIN-125® (phenytoin) oral suspension
Initial U.S. Approval: 1953

1 INDICATIONS AND USAGE

DILANTIN is indicated for the treatment of tonic-clonic (grand mal) and psychomotor (temporal lobe) seizures. (1)

2 DOSAGE AND ADMINISTRATION

- Adult starting dose in patients who have received no previous treatment is 5 mL three times daily, with dose adjustments as necessary, up to 25 mL daily. (2.2)
- Pediatric starting dose is 5 mg/kg/day in two to three equally divided doses, with dosage adjustments as necessary, up to a maximum of 300 mg daily. Maintenance dosage is 4 to 8 mg/kg/day. (2.3)
- Serum blood level determinations may be necessary for optimal dosage adjustments—the clinically effective serum total concentration is 10 to 20 mcg/mL (unbound phenytoin concentration is 1 to 2 mcg/mL). (2.1)

3 DOSAGE FORMS AND STRENGTHS

DILANTIN-125 is available as a 125 mg phenytoin/5 mL oral suspension. (3)

4 CONTRAINDICATIONS

- Hypersensitivity to phenytoin, its ingredients, or other hydantoins (4, 5.5)
- A history of prior acute hepatotoxicity attributable to phenytoin (4, 5.8)
- Coadministration with delavirdine (4)

5 WARNINGS AND PRECAUTIONS

- Withdrawal Precipitated Seizure: May precipitate status epilepticus. Dose reductions or discontinuation should be done gradually. (5.1)
- Suicidal Behavior and Ideation: Monitor patients for the emergence or worsening of depression, suicidal thoughts or behavior, and/or any unusual changes in mood or behavior. (5.2)
- Serious Dermatologic Reactions: Discontinue DILANTIN at the first sign of a rash, unless the rash is clearly not drug-related. If signs or symptoms suggest SJS/TEN, use of this drug should not be resumed and alternative therapy should be considered. (5.3)
- Drug Reaction with Eosinophilia and Systemic Symptoms (DRESS)/Multiorgan Hypersensitivity: If signs or symptoms of hypersensitivity are present, evaluate the patient immediately. Discontinue if an alternative etiology cannot be established. (5.4)
- Cardiac Effects: Bradycardia and cardiac arrest have been reported. (5.6)
- Angioedema: Discontinue immediately if symptoms of angioedema such as facial, perioral, or upper airway swelling occur. (5.7)
- Hepatic Injury: Cases of acute hepatotoxicity have been reported with DILANTIN. If this occurs, immediately discontinue. (4, 5.8)
- Hematopoietic Complications: If occurs, follow-up observation is indicated and an alternative antiepileptic treatment should be used. (5.9)

6 ADVERSE REACTIONS

The most common adverse reactions are nervous system reactions, including nystagmus, ataxia, slurred speech, decreased coordination, somnolence, and mental confusion. (6)

To report SUSPECTED ADVERSE REACTIONS, contact Viatris at 1-877-446-3679 (1-877-4-INFO-RX) or FDA at 1-800-FDA-1088 or www.fda.gov/medwatch.

7 DRUG INTERACTIONS

Multiple drug interactions because of extensive plasma protein binding, saturable metabolism and potent induction of hepatic enzymes. (7.1, 7.2)

8 USE IN SPECIFIC POPULATIONS

- Pregnancy: Prenatal exposure may increase the risks for congenital malformations and other adverse developmental outcomes. (5.13, 8.1)
- Renal and/or Hepatic Impairment or Hypoalbuminemia: Monitor unbound phenytoin concentrations in these patients. (8.6)

FULL PRESCRIBING INFORMATION

1 INDICATIONS AND USAGE

DILANTIN is indicated for the treatment of tonic-clonic (grand mal) and psychomotor (temporal lobe) seizures.

2 DOSAGE AND ADMINISTRATION

2.1 Important Administration Instructions

FOR ORAL ADMINISTRATION ONLY; NOT FOR PARENTERAL USE

A calibrated measuring device is recommended to measure and deliver the prescribed dose accurately. A household teaspoon or tablespoon is not an adequate measuring device.

2.2 Adult Dosage

The recommended starting dosage for adult patients who have received no previous treatment is 5 mL (125 mg/5 mL), or one teaspoonful, by mouth three times daily. Adjust the dosage to suit individual requirements, up to a maximum of 25 mL daily [see Dosage and Administration (2.4)].

2.3 Pediatric Dosage

The recommended starting dosage for pediatric patients is 5 mg/kg/day by mouth in two or three equally divided doses, with subsequent dosage individualized to a maximum of 300 mg daily in divided doses. A recommended daily maintenance dosage is usually 4 to 8 mg/kg/day in equally divided doses. Children over 6 years and adolescents may require the minimum adult dosage (300 mg/day).

2.4 Dosage Adjustments

Dosage should be individualized to provide maximum benefit. In some cases, serum blood level determinations may be necessary for optimal dosage adjustments. Trough levels provide information about clinically effective serum level range and confirm patient compliance, and are obtained just prior to the patient’s next scheduled dose. Peak levels indicate an individual’s threshold for emergence of dose-related side effects and are obtained at the time of expected peak concentration. Therapeutic effect without clinical signs of toxicity occurs more often with serum total concentrations between 10 and 20 mcg/mL (unbound phenytoin concentrations of 1 to 2 mcg/mL), although some mild cases of tonic-clonic (grand mal) epilepsy may be controlled with lower serum levels of phenytoin. In patients with renal or hepatic disease, or in those with hypoalbuminemia, the monitoring of unbound phenytoin concentrations may be more relevant [see Dosage and Administration (2.6)].

With recommended dosages, a period of seven to ten days may be required to achieve phenytoin steady-state blood levels, and changes in dosage (increase or decrease) should not be carried out at intervals shorter than seven to ten days.

2.5 Switching Between Phenytoin Formulations

The free acid form of phenytoin is used in DILANTIN-125 Suspension and DILANTIN Infatabs. DILANTIN extended capsules and parenteral DILANTIN are formulated with the sodium salt of phenytoin. Because there is approximately an 8% increase in drug content with the free acid form over that of the sodium salt, dosage adjustments and serum level monitoring may be necessary when switching from a product formulated with the free acid to a product formulated with the sodium salt and vice versa.

2.6 Dosing in Patients with Renal or Hepatic Impairment or Hypoalbuminemia

Because the fraction of unbound phenytoin is increased in patients with renal or hepatic disease, or in those with hypoalbuminemia, the monitoring of phenytoin serum levels should be based on the unbound fraction in those patients [see Warnings and Precautions (5.11) and Use in Specific Populations (8.6)].

2.7 Geriatric Dosage

Phenytoin clearance is decreased slightly in elderly patients and lower or less frequent dosing may be required [see Clinical Pharmacology (12.3)].

2.8 Dosing during Pregnancy

Decreased serum concentrations of phenytoin may occur during pregnancy because of altered phenytoin pharmacokinetics. Periodic measurement of serum phenytoin concentrations should be performed during pregnancy, and the DILANTIN dosage should be adjusted as necessary. Postpartum restoration of the original dosage will probably be indicated [see Use in Specific Populations (8.1)]. Because of potential changes in protein binding during pregnancy, the monitoring of phenytoin serum levels should be based on the unbound fraction.

3 DOSAGE FORMS AND STRENGTHS

DILANTIN-125 is available as a 125 mg phenytoin/5 mL oral suspension of orange color with an orange-vanilla flavor.

4 CONTRAINDICATIONS

DILANTIN is contraindicated in patients with:

- A history of hypersensitivity to phenytoin, its inactive ingredients, or other hydantoins [see Warnings and Precautions (5.5)]. Reactions have included angioedema.
- A history of prior acute hepatotoxicity attributable to phenytoin [see Warnings and Precautions (5.8)].
- Coadministration with delavirdine because of the potential for loss of virologic response and possible resistance to delavirdine or to the class of non-nucleoside reverse transcriptase inhibitors.

5 WARNINGS AND PRECAUTIONS

5.1 Withdrawal Precipitated Seizure, Status Epilepticus

Abrupt withdrawal of phenytoin in epileptic patients may precipitate status epilepticus. When in the judgment of the clinician the need for dosage reduction, discontinuation, or substitution of alternative anticonvulsant medication arises, this should be done gradually. However, in the event of an allergic or hypersensitivity reaction, more rapid substitution of alternative therapy may be necessary. In this case, alternative therapy should be an anticonvulsant not belonging to the hydantoin chemical class.

5.2 Suicidal Behavior and Ideation

Antiepileptic drugs (AEDs), including DILANTIN, increase the risk of suicidal thoughts or behavior in patients taking these drugs for any indication. Patients treated with any AED for any indication should be monitored for the emergence or worsening of depression, suicidal thoughts or behavior, and/or any unusual changes in mood or behavior.

Pooled analyses of 199 placebo-controlled clinical trials (mono- and adjunctive therapy) of 11 different AEDs showed that patients randomized to one of the AEDs had approximately twice the risk (adjusted Relative Risk 1.8, 95% CI:1.2, 2.7) of suicidal thinking or behavior compared to patients randomized to placebo. In these trials, which had a median treatment duration of 12 weeks, the estimated incidence rate of suicidal behavior or ideation among 27,863 AED-treated patients was 0.43%, compared to 0.24% among 16,029 placebo-treated patients, representing an increase of approximately one case of suicidal thinking or behavior for every 530 patients treated. There were four suicides in drug-treated patients in the trials and none in placebo-treated patients, but the number is too small to allow any conclusion about drug effect on suicide.

The increased risk of suicidal thoughts or behavior with AEDs was observed as early as one week after starting drug treatment with AEDs and persisted for the duration of treatment assessed. Because most trials included in the analysis did not extend beyond 24 weeks, the risk of suicidal thoughts or behavior beyond 24 weeks could not be assessed.

The risk of suicidal thoughts or behavior was generally consistent among drugs in the data analyzed. The finding of increased risk with AEDs of varying mechanisms of action and across a range of indications suggests that the risk applies to all AEDs used for any indication. The risk did not vary substantially by age (5 to 100 years) in the clinical trials analyzed.

Table 1 shows absolute and relative risk by indication for all evaluated AEDs.

Table 1: Risk by Indication for Antiepileptic Drugs in the Pooled Analysis
Indication | Placebo Patients with Events Per 1000 Patients | Drug Patients with Events Per 1000 Patients | Relative Risk: Incidence of Events in Drug Patients/Incidence in Placebo Patients | Risk Difference: Additional Drug Patients with Events Per 1000 Patients
Epilepsy | 1.0 | 3.4 | 3.5 | 2.4
Psychiatric | 5.7 | 8.5 | 1.5 | 2.9
Other | 1.0 | 1.8 | 1.9 | 0.9
Total | 2.4 | 4.3 | 1.8 | 1.9

The relative risk for suicidal thoughts or behavior was higher in clinical trials for epilepsy than in clinical trials for psychiatric or other conditions, but the absolute risk differences were similar for the epilepsy and psychiatric indications.

Anyone considering prescribing DILANTIN or any other AED must balance the risk of suicidal thoughts or behavior with the risk of untreated illness. Epilepsy and many other illnesses for which AEDs are prescribed are themselves associated with morbidity and mortality and an increased risk of suicidal thoughts and behavior. Should suicidal thoughts and behavior emerge during treatment, the prescriber needs to consider whether the emergence of these symptoms in any given patient may be related to the illness being treated.

Patients, their caregivers, and families should be informed that AEDs increase the risk of suicidal thoughts and behavior and should be advised of the need to be alert for the emergence or worsening of the signs and symptoms of depression, any unusual changes in mood or behavior, or the emergence of suicidal thoughts, behavior, or thoughts about self-harm. Behaviors of concern should be reported immediately to healthcare providers.

5.3 Serious Dermatologic Reactions

DILANTIN can cause severe cutaneous adverse reactions (SCARs), which may be fatal. Reported reactions in phenytoin-treated patients have included toxic epidermal necrolysis (TEN), Stevens-Johnson syndrome (SJS), acute generalized exanthematous pustulosis (AGEP), and Drug Reaction with Eosinophilia and Systemic Symptoms (DRESS) [see Warnings and Precautions (5.4)]. The onset of symptoms is usually within 28 days, but can occur later. DILANTIN should be discontinued at the first sign of a rash, unless the rash is clearly not drug-related. If signs or symptoms suggest a severe cutaneous adverse reaction, use of this drug should not be resumed and alternative therapy should be considered. If a rash occurs, the patient should be evaluated for signs and symptoms of SCARs.

Studies in patients of Chinese ancestry have found a strong association between the risk of developing SJS/TEN and the presence of HLA-B*1502, an inherited allelic variant of the HLA B gene, in patients using carbamazepine. Limited evidence suggests that HLA-B*1502 may be a risk factor for the development of SJS/TEN in patients of Asian ancestry taking other antiepileptic drugs associated with SJS/TEN, including phenytoin. In addition, retrospective, case-control, genome-wide association studies in patients of southeast Asian ancestry have also identified an increased risk of SCARs in carriers of the decreased function CYP2C9*3 variant, which has also been associated with decreased clearance of phenytoin. Consider avoiding DILANTIN as an alternative to carbamazepine in patients who are positive for HLA-B*1502 or in CYP2C9*3 carriers [see Use in Specific Populations (8.7) and Clinical Pharmacology (12.5)].

The use of HLA-B*1502 or CYP2C9 genotyping has important limitations and must never substitute for appropriate clinical vigilance and patient management. The role of other possible factors in the development of, and morbidity from, SJS/TEN, such as antiepileptic drug (AED) dose, compliance, concomitant medications, comorbidities, and the level of dermatologic monitoring have not been studied.

5.4 Drug Reaction with Eosinophilia and Systemic Symptoms (DRESS)/Multiorgan Hypersensitivity

Drug Reaction with Eosinophilia and Systemic Symptoms (DRESS), also known as Multiorgan hypersensitivity, has been reported in patients taking antiepileptic drugs, including DILANTIN. Some of these events have been fatal or life-threatening. DRESS typically, although not exclusively, presents with fever, rash, lymphadenopathy, and/or facial swelling, in association with other organ system involvement, such as hepatitis, nephritis, hematological abnormalities, myocarditis, or myositis sometimes resembling an acute viral infection. Eosinophilia is often present. Because this disorder is variable in its expression, other organ systems not noted here may be involved. It is important to note that early manifestations of hypersensitivity, such as fever or lymphadenopathy, may be present even though rash is not evident. If such signs or symptoms are present, the patient should be evaluated immediately. DILANTIN should be discontinued if an alternative etiology for the signs or symptoms cannot be established.

5.5 Hypersensitivity

DILANTIN and other hydantoins are contraindicated in patients who have experienced phenytoin hypersensitivity [see Contraindications (4) and Warnings and Precautions (5.7)]. Additionally, consider alternatives to structurally similar drugs such as carboxamides (e.g., carbamazepine), barbiturates, succinimides, and oxazolidinediones (e.g., trimethadione) in these same patients. Similarly, if there is a history of hypersensitivity reactions to these structurally similar drugs in the patient or immediate family members, consider alternatives to DILANTIN.

5.6 Cardiac Effects

Cases of bradycardia and cardiac arrest have been reported in DILANTIN-treated patients, both at recommended phenytoin doses and levels, and in association with phenytoin toxicity [see Overdosage (10)]. Most of the reports of cardiac arrest occurred in patients with underlying cardiac disease.

5.7 Angioedema

Angioedema has been reported in patients treated with DILANTIN in the postmarketing setting. DILANTIN should be discontinued immediately if symptoms of angioedema, such as facial, perioral, or upper airway swelling occur. DILANTIN should be discontinued permanently if a clear alternative etiology for the reaction cannot be established.

5.8 Hepatic Injury

Cases of acute hepatotoxicity, including infrequent cases of acute hepatic failure, have been reported with DILANTIN. These events may be part of the spectrum of DRESS or may occur in isolation [see Warnings and Precautions (5.4)]. Other common manifestations include jaundice, hepatomegaly, elevated serum transaminase levels, leukocytosis, and eosinophilia. The clinical course of acute phenytoin hepatotoxicity ranges from prompt recovery to fatal outcomes. In these patients with acute hepatotoxicity, DILANTIN should be immediately discontinued and not readministered.

5.9 Hematopoietic Complications

Hematopoietic complications, some fatal, have occasionally been reported in association with administration of DILANTIN. These have included thrombocytopenia, leukopenia, granulocytopenia, agranulocytosis, and pancytopenia with or without bone marrow suppression.

There have been a number of reports suggesting a relationship between phenytoin and the development of lymphadenopathy (local or generalized) including benign lymph node hyperplasia, pseudolymphoma, lymphoma, and Hodgkin’s disease. Although a cause and effect relationship has not been established, the occurrence of lymphadenopathy indicates the need to differentiate such a condition from other types of lymph node pathology. Lymph node involvement may occur with or without symptoms and signs of DRESS [see Warnings and Precautions (5.4)].

In all cases of lymphadenopathy, follow-up observation for an extended period is indicated and every effort should be made to achieve seizure control using alternative antiepileptic drugs.

5.10 Effects on Vitamin D and Bone

The chronic use of phenytoin in patients with epilepsy has been associated with decreased bone mineral density (osteopenia, osteoporosis, and osteomalacia) and bone fractures. Phenytoin induces hepatic metabolizing enzymes. This may enhance the metabolism of vitamin D and decrease vitamin D levels, which may lead to vitamin D deficiency, hypocalcemia, and hypophosphatemia. Consideration should be given to screening with bone-related laboratory and radiological tests as appropriate and initiating treatment plans according to established guidelines.

5.11 Renal or Hepatic Impairment, or Hypoalbuminemia

Because the fraction of unbound phenytoin is increased in patients with renal or hepatic disease, or in those with hypoalbuminemia, the monitoring of phenytoin serum levels should be based on the unbound fraction in those patients.

5.12 Exacerbation of Porphyria

In view of isolated reports associating phenytoin with exacerbation of porphyria, caution should be exercised in using this medication in patients suffering from this disease.

5.13 Teratogenicity and Other Harm to the Newborn

DILANTIN may cause fetal harm when administered to a pregnant woman. Prenatal exposure to phenytoin may increase the risks for congenital malformations and other adverse developmental outcomes [see Use in Specific Populations (8.1)].

Increased frequencies of major malformations (such as orofacial clefts and cardiac defects), and abnormalities characteristic of fetal hydantoin syndrome, including dysmorphic skull and facial features, nail and digit hypoplasia, growth abnormalities (including microcephaly), and cognitive deficits, have been reported among children born to epileptic women who took phenytoin alone or in combination with other antiepileptic drugs during pregnancy. There have been several reported cases of malignancies, including neuroblastoma.

A potentially life-threatening bleeding disorder related to decreased levels of vitamin K-dependent clotting factors may occur in newborns exposed to phenytoin in utero. This drug-induced condition can be prevented with vitamin K administration to the mother before delivery and to the neonate after birth.

5.14 Hyperglycemia

Hyperglycemia, resulting from the drug’s inhibitory effects on insulin release, has been reported. Phenytoin may also raise the serum glucose level in diabetic patients.

5.15 Serum Phenytoin Levels above Therapeutic Range

Serum levels of phenytoin sustained above the therapeutic range may produce confusional states referred to as “delirium,” “psychosis,” or “encephalopathy,” or rarely irreversible cerebellar dysfunction and/or cerebellar atrophy. Accordingly, at the first sign of acute toxicity, serum levels should be immediately checked. Dose reduction of phenytoin therapy is indicated if serum levels are excessive; if symptoms persist, termination is recommended.

6 ADVERSE REACTIONS

The following serious adverse reactions are described elsewhere in the labeling:

- Withdrawal Precipitated Seizure, Status Epilepticus [see Warnings and Precautions (5.1)]
- Suicidal Behavior and Ideation [see Warnings and Precautions (5.2)]
- Serious Dermatologic Reactions [see Warnings and Precautions (5.3)]
- Drug Reaction with Eosinophilia and Systemic Symptoms (DRESS)/Multiorgan Hypersensitivity [see Warnings and Precautions (5.4)]
- Hypersensitivity [see Warnings and Precautions (5.5)]
- Cardiac Effects [see Warnings and Precautions (5.6)]
- Angioedema [see Warnings and Precautions (5.7)]
- Hepatic Injury [see Warnings and Precautions (5.8)]
- Hematopoietic Complications [see Warnings and Precautions (5.9)]
- Effects on Vitamin D and Bone [see Warnings and Precautions (5.10)]
- Exacerbation of Porphyria [see Warnings and Precautions (5.12)]
- Teratogenicity and Other Harm to the Newborn [see Warnings and Precautions (5.13)]
- Hyperglycemia [see Warnings and Precautions (5.14)]

The following adverse reactions associated with the use of DILANTIN were identified in clinical studies or postmarketing reports. Because these reactions are reported voluntarily from a population of uncertain size, it is not always possible to reliably estimate their frequency or establish a causal relationship to drug exposure.

Body as a Whole: Allergic reactions in the form of rash and rarely more serious forms and DRESS have been observed, as has angioedema [see Warnings and Precautions (5.3, 5.4, 5.7)]. Anaphylaxis has also been reported.

There have also been reports of coarsening of facial features, systemic lupus erythematosus, periarteritis nodosa, and immunoglobulin abnormalities.

Digestive System: Acute hepatic failure, toxic hepatitis, liver damage, nausea, vomiting, constipation, enlargement of the lips, and gingival hyperplasia.

Hematologic and Lymphatic System: Hematopoietic complications, some fatal, have occasionally been reported in association with administration of phenytoin. These have included thrombocytopenia, leukopenia, granulocytopenia, agranulocytosis, and pancytopenia with or without bone marrow suppression. While macrocytosis and megaloblastic anemia have occurred, these conditions usually respond to folic acid therapy. Lymphadenopathy including benign lymph node hyperplasia, pseudolymphoma, lymphoma, and Hodgkin’s disease have been reported [see Warnings and Precautions (5.9)]. Pure red cell aplasia has also been reported.

Laboratory Test Abnormality: Phenytoin may decrease serum concentrations of thyroid hormone (T4 and T3), sometimes with an accompanying increase in thyroid-stimulating hormone (TSH), but usually in the absence of clinical hypothyroidism. Phenytoin may also produce lower than normal values for dexamethasone or metyrapone tests. Phenytoin may cause increased serum levels of glucose [see Warnings and Precautions (5.14)], alkaline phosphatase, and gamma glutamyl transpeptidase (GGT).

Nervous System: The most common adverse reactions encountered with phenytoin therapy are nervous system reactions and are usually dose-related. Reactions include nystagmus, ataxia, slurred speech, decreased coordination, somnolence, and mental confusion. Dizziness, vertigo, insomnia, transient nervousness, motor twitchings, paresthesias, and headaches have also been observed. There have also been rare reports of phenytoin-induced dyskinesias, including chorea, dystonia, tremor and asterixis, similar to those induced by phenothiazine and other neuroleptic drugs. Cerebellar atrophy has been reported, and appears more likely in settings of elevated phenytoin levels and/or long-term phenytoin use [see Warnings and Precautions (5.15)].

A predominantly sensory peripheral polyneuropathy has been observed in patients receiving long-term phenytoin therapy.

Skin and Appendages: Dermatological manifestations sometimes accompanied by fever have included scarlatiniform or morbilliform rashes. A morbilliform rash (measles-like) is the most common; other types of dermatitis are seen more rarely. Other more serious forms which may be fatal have included bullous, exfoliative or purpuric dermatitis, acute generalized exanthematous pustulosis, Stevens-Johnson syndrome, and toxic epidermal necrolysis [see Warnings and Precautions (5.3)]. There have also been reports of hypertrichosis and urticaria.

Special Senses: Altered taste sensation including metallic taste.

Urogenital: Peyronie’s disease.

7 DRUG INTERACTIONS

Phenytoin is extensively bound to plasma proteins and is prone to competitive displacement. Phenytoin is primarily metabolized by the hepatic cytochrome P450 enzyme CYP2C9 and to a lesser extent by CYP2C19 and is particularly susceptible to inhibitory drug interactions because it is subject to saturable metabolism. Inhibition of metabolism may produce significant increases in circulating phenytoin concentrations and enhance the risk of drug toxicity. Monitoring of phenytoin serum levels is recommended when a drug interaction is suspected.

Phenytoin is a potent inducer of hepatic drug-metabolizing enzymes.

7.1 Drugs that Affect Phenytoin Concentrations

Table 2 includes commonly occurring drug interactions that affect phenytoin concentrations. However, this list is not intended to be inclusive or comprehensive. Individual prescribing information from relevant drugs should be consulted.

The addition or withdrawal of these agents in patients on phenytoin therapy may require an adjustment of the phenytoin dose to achieve optimal clinical outcome.

Table 2: Drugs That Affect Phenytoin Concentrations
Interacting Agent | Examples
Drugs that may increase phenytoin serum levels
Antiepileptic drugs | Ethosuximide, felbamate, oxcarbazepine, methsuximide, topiramate
Azoles | Fluconazole, ketoconazole, itraconazole, miconazole, voriconazole
Antineoplastic agents | Capecitabine, fluorouracil
Antidepressants | Fluoxetine, fluvoxamine, sertraline
Gastric acid reducing agents | H2 antagonists (cimetidine), omeprazole
Sulfonamides | Sulfamethizole, sulfaphenazole, sulfadiazine, sulfamethoxazole-trimethoprim
Other | Acute alcohol intake, amiodarone, chloramphenicol, chlordiazepoxide, disulfiram, estrogen, fluvastatin, isoniazid, methylphenidate, phenothiazines, salicylates, ticlopidine, tolbutamide, trazodone, warfarin
Drugs that may decrease phenytoin serum levels
Antacids [Antacids may affect absorption of phenytoin.] | Calcium carbonate, aluminum hydroxide, magnesium hydroxide Prevention or Management: Phenytoin and antacids should not be taken at the same time of day
Antineoplastic agents (usually in combination) | Bleomycin, carboplatin, cisplatin, doxorubicin, methotrexate
Antiviral agents | Fosamprenavir, nelfinavir, ritonavir
Antiepileptic drugs | Carbamazepine, vigabatrin
Other | Chronic alcohol abuse, diazepam, diazoxide, folic acid, reserpine, rifampin, St. John’s wort [The induction potency of St. John’s wort may vary widely based on preparation.] , sucralfate, theophylline
Drugs that may either increase or decrease phenytoin serum levels
Antiepileptic drugs | Phenobarbital, valproate sodium [Valproate sodium and valproic acid are similar medications. The term valproate has been used to represent these medications.] , valproic acid

7.2 Drugs Affected by Phenytoin

Table 3 includes commonly occurring drug interactions affected by phenytoin. However, this list is not intended to be inclusive or comprehensive. Individual drug package inserts should be consulted.

The addition or withdrawal of phenytoin during concomitant therapy with these agents may require adjustment of the dose of these agents to achieve optimal clinical outcome.

Table 3: Drugs Affected by Phenytoin
Interacting Agent | Examples
Drugs whose efficacy is impaired by phenytoin
Azoles | Fluconazole, ketoconazole, itraconazole, posaconazole, voriconazole
Antineoplastic agents | Irinotecan, paclitaxel, teniposide
Delavirdine | Phenytoin can substantially reduce the concentrations of delavirdine. This can lead to loss of virologic response and possible resistance [see Contraindications (4)].
Neuromuscular blocking agents | Cisatracurium, pancuronium, rocuronium and vecuronium: resistance to the neuromuscular blocking action of the nondepolarizing neuromuscular blocking agents has occurred in patients chronically administered phenytoin. Whether or not phenytoin has the same effect on other non-depolarizing agents is unknown. Prevention or Management: Patients should be monitored closely for more rapid recovery from neuromuscular blockade than expected, and infusion rate requirements may be higher.
Warfarin | Increased and decreased PT/INR responses have been reported when phenytoin is coadministered with warfarin
Other | Corticosteroids, doxycycline, estrogens, furosemide, oral contraceptives, paroxetine, quinidine, rifampin, sertraline, theophylline, and vitamin D
Drugs whose level is decreased by phenytoin
Anticoagulants | Apixaban, dabigatran, edoxaban, rivaroxaban
Antiepileptic drugs [The effect of phenytoin on phenobarbital, valproic acid and sodium valproate serum levels is unpredictable.] | Carbamazepine, felbamate, lamotrigine, topiramate, oxcarbazepine, lacosamide
Antilipidemic agents | Atorvastatin, fluvastatin, simvastatin
Antiplatelets | Ticagrelor
Antiviral agents | Efavirenz, lopinavir/ritonavir, indinavir, nelfinavir, ritonavir, saquinavir Fosamprenavir: phenytoin when given with fosamprenavir alone may decrease the concentration of amprenavir, the active metabolite. Phenytoin when given with the combination of fosamprenavir and ritonavir may increase the concentration of amprenavir
Calcium channel blockers | Nifedipine, nimodipine, nisoldipine, verapamil
Other | Albendazole (decreases active metabolite), chlorpropamide, clozapine, cyclosporine, digoxin, disopyramide, folic acid, methadone, mexiletine, praziquantel, quetiapine

7.3 Hyperammonemia with Concomitant Use of Valproate

Concomitant administration of phenytoin and valproate has been associated with an increased risk of valproate-associated hyperammonemia. Patients treated concomitantly with these two drugs should be monitored for signs and symptoms of hyperammonemia.

7.4 Drug Enteral Feeding/Nutritional Preparations Interaction

Literature reports suggest that patients who have received enteral feeding preparations and/or related nutritional supplements have lower than expected phenytoin serum levels. It is therefore suggested that phenytoin not be administered concomitantly with an enteral feeding preparation. More frequent serum phenytoin level monitoring may be necessary in these patients.

7.5 Drug/Laboratory Test Interactions

Care should be taken when using immunoanalytical methods to measure serum phenytoin concentrations.

8 USE IN SPECIFIC POPULATIONS

8.1 Pregnancy

Pregnancy Exposure Registry

There is a pregnancy exposure registry that monitors pregnancy outcomes in women exposed to antiepileptic drugs (AEDs), such as DILANTIN, during pregnancy. Physicians are advised to recommend that pregnant patients taking DILANTIN enroll in the North American Antiepileptic Drug (NAAED) Pregnancy Registry. This can be done by calling the tollfree number 1-888-233-2334, and must be done by patients themselves. Information on the registry can also be found at the website http://www.aedpregnancyregistry.org/.

Risk Summary

In humans, prenatal exposure to phenytoin may increase the risks for congenital malformations and other adverse developmental outcomes. Prenatal phenytoin exposure is associated with an increased incidence of major malformations, including orofacial clefts and cardiac defects. In addition, the fetal hydantoin syndrome, a pattern of abnormalities including dysmorphic skull and facial features, nail and digit hypoplasia, growth abnormalities (including microcephaly), and cognitive deficits has been reported among children born to epileptic women who took phenytoin alone or in combination with other antiepileptic drugs during pregnancy [see Data]. There have been several reported cases of malignancies, including neuroblastoma, in children whose mothers received phenytoin during pregnancy.

Administration of phenytoin to pregnant animals resulted in an increased incidence of fetal malformations and other manifestations of developmental toxicity (including embryofetal death, growth impairment, and behavioral abnormalities) in multiple species at clinically relevant doses [see Data].

In the U.S. general population, the estimated background risk of major birth defects and of miscarriage in clinically recognized pregnancies is 2 to 4% and 15 to 20%, respectively. The background risk of major birth defects and miscarriage for the indicated population is unknown.

Clinical Considerations

Disease-associated maternal risk

An increase in seizure frequency may occur during pregnancy because of altered phenytoin pharmacokinetics. Periodic measurement of serum phenytoin concentrations may be valuable in the management of pregnant women as a guide to appropriate adjustment of dosage [see Dosage and Administration (2.4, 2.8)]. However, postpartum restoration of the original dosage will probably be indicated [see Clinical Pharmacology (12.3)].

Fetal/Neonatal Adverse Reactions

A potentially life-threatening bleeding disorder related to decreased levels of vitamin K-dependent clotting factors may occur in newborns exposed to phenytoin in utero. This drug-induced condition can be prevented with vitamin K administration to the mother before delivery and to the neonate after birth.

Data

Human Data

Meta-analyses using data from published observational studies and registries have estimated an approximately 2.4-fold increased risk for any major malformation in children with prenatal phenytoin exposure compared to controls. An increased risk of heart defects, facial clefts, and digital hypoplasia has been reported. The fetal hydantoin syndrome is a pattern of congenital anomalies including craniofacial anomalies, nail and digital hypoplasia, prenatal-onset growth deficiency, and neurodevelopmental deficiencies.

Animal Data

Administration of phenytoin to pregnant rats, rabbits, and mice during organogenesis resulted in embryofetal death, fetal malformations, and decreased fetal growth. Malformations (including craniofacial, cardiovascular, neural, limb, and digit abnormalities) were observed in rats, rabbits, and mice at doses as low as 100, 75, and 12.5 mg/kg, respectively.

8.2 Lactation

Risk Summary

Phenytoin is secreted in human milk. The developmental and health benefits of breastfeeding should be considered along with the mother’s clinical need for DILANTIN and any potential adverse effects on the breastfed infant from DILANTIN or from the underlying maternal condition.

8.4 Pediatric Use

Initially, 5 mg/kg/day in two or three equally divided doses, with subsequent dosage individualized to a maximum of 300 mg daily. A recommended daily maintenance dosage is usually 4 to 8 mg/kg. Children over 6 years and adolescents may require the minimum adult dosage (300 mg/day) [see Dosage and Administration (2.3)].

8.5 Geriatric Use

Phenytoin clearance tends to decrease with increasing age [see Clinical Pharmacology (12.3)]. Lower or less frequent dosing may be required [see Dosage and Administration (2.7)].

8.6 Renal and/or Hepatic Impairment or Hypoalbuminemia

The liver is the chief site of biotransformation of phenytoin; patients with impaired liver function, elderly patients, or those who are gravely ill may show early signs of toxicity.

Because the fraction of unbound phenytoin is increased in patients with renal or hepatic disease, or in those with hypoalbuminemia, the monitoring of phenytoin serum levels should be based on the unbound fraction in those patients.

8.7 Use in Patients with Decreased CYP2C9 Function

Patients who are intermediate or poor metabolizers of CYP2C9 substrates (e.g., *1/*3, *2/*2, *3/*3) may exhibit increased phenytoin serum concentrations compared to patients who are normal metabolizers (e.g., *1/*1). Thus, patients who are known to be intermediate or poor metabolizers may ultimately require lower doses of phenytoin to maintain similar steady-state concentrations compared to normal metabolizers. If early signs of dose-related central nervous system (CNS) toxicity develop, serum concentrations should be checked immediately [see Clinical Pharmacology (12.5)].

10 OVERDOSAGE

The lethal dose in pediatric patients is not known. The lethal dose in adults is estimated to be 2 to 5 grams. The initial symptoms are nystagmus, ataxia, and dysarthria. Other signs are tremor, hyperreflexia, lethargy, slurred speech, blurred vision, nausea, and vomiting. The patient may become comatose and hypotensive. Bradycardia and cardiac arrest have been reported [see Warnings and Precautions (5.6)]. Death is caused by respiratory and circulatory depression.

There are marked variations among individuals with respect to phenytoin serum levels where toxicity may occur. Nystagmus, on lateral gaze, usually appears at 20 mcg/mL, ataxia at 30 mcg/mL, dysarthria and lethargy appear when the serum concentration is over 40 mcg/mL, but as high a concentration as 50 mcg/mL has been reported without evidence of toxicity. As much as 25 times the therapeutic dose has been taken to result in a serum concentration over 100 mcg/mL with complete recovery. Irreversible cerebellar dysfunction and atrophy have been reported.

Treatment: Treatment is nonspecific since there is no known antidote.

The adequacy of the respiratory and circulatory systems should be carefully observed and appropriate supportive measures employed. Hemodialysis can be considered since phenytoin is not completely bound to plasma proteins. Total exchange transfusion has been used in the treatment of severe intoxication in pediatric patients.

In acute overdosage the possibility of other CNS depressants, including alcohol, should be borne in mind.

11 DESCRIPTION

DILANTIN (phenytoin) is related to the barbiturates in chemical structure, but has a five-membered ring. The chemical name is 5,5-diphenyl-2,4 imidazolidinedione, having the following structural formula:

Each 5 mL of the oral suspension contains 125 mg of phenytoin, USP; alcohol, USP (maximum content not greater than 0.6 percent); banana flavor; carboxymethylcellulose sodium, USP; citric acid, anhydrous, USP; glycerin, USP; magnesium aluminum silicate, NF; orange oil concentrate; polysorbate 40, NF; purified water, USP; sodium benzoate, NF; sucrose, NF; vanillin, NF; and FD&C yellow No. 6.

12 CLINICAL PHARMACOLOGY

12.1 Mechanism of Action

The precise mechanism by which phenytoin exerts its therapeutic effect has not been established but is thought to involve the voltage-dependent blockade of membrane sodium channels resulting in a reduction in sustained high-frequency neuronal discharges.

12.3 Pharmacokinetics

Absorption

For DILANTIN-125 Suspension, peak levels occur 1½ to 3 hours after administration. Steady-state therapeutic levels are achieved at least 7 to 10 days (5 to 7 half-lives) after initiation of therapy with recommended doses of 300 mg/day. When serum level determinations are necessary, they should be obtained at least 5 to 7 half-lives after treatment initiation, dosage change, or addition or subtraction of another drug to the regimen so that equilibrium or steady-state will have been achieved.

Distribution

Phenytoin is extensively bound to serum plasma proteins.

Elimination

The plasma half-life in man after oral administration of phenytoin averages 22 hours, with a range of 7 to 42 hours.

Metabolism

Phenytoin is primarily metabolized by the hepatic cytochrome P450 enzyme CYP2C9 and to a lesser extent by CYP2C19. Because phenytoin is hydroxylated in the liver by an enzyme system which is saturable at high serum levels, small incremental doses may increase the half-life and produce very substantial increases in serum levels, when these are in the upper range. The steady-state level may be disproportionately increased, with resultant intoxication, from an increase in dosage of 10% or more.

In most patients maintained at a steady dosage, stable phenytoin serum levels are achieved. There may be wide interpatient variability in phenytoin serum levels with equivalent dosages. Patients with unusually low levels may be noncompliant or hypermetabolizers of phenytoin. Unusually high levels result from liver disease, variant CYP2C9 and CYP2C19 alleles, or drug interactions which result in metabolic interference. The patient with large variations in phenytoin serum levels, despite standard doses, presents a difficult clinical problem. Serum level determinations in such patients may be particularly helpful. As phenytoin is highly protein bound, free phenytoin levels may be altered in patients whose protein binding characteristics differ from normal.

Excretion

Most of the drug is excreted in the bile as inactive metabolites which are then reabsorbed from the intestinal tract and excreted in the urine. Urinary excretion of phenytoin and its metabolites occurs partly with glomerular filtration but, more importantly, by tubular secretion.

Specific Populations

Age: Geriatric Population:

Phenytoin clearance tends to decrease with increasing age (20% less in patients over 70 years of age relative to that in patients 20 to 30 years of age). Since phenytoin clearance is decreased slightly in elderly patients, lower or less frequent dosing may be required [see Dosage and Administration (2.7)].

Sex/Race:

Gender and race have no significant impact on phenytoin pharmacokinetics.

Renal or Hepatic Impairment:

Increased fraction of unbound phenytoin in patients with renal or hepatic disease, or in those with hypoalbuminemia has been reported.

Pregnancy:

It has been reported in the literature that the plasma clearance of phenytoin generally increased during pregnancy, reached a peak in the third trimester and returned to the level of pre-pregnancy after few weeks or months of delivery.

Drug Interaction Studies

Phenytoin is primarily metabolized by the hepatic cytochrome P450 enzyme CYP2C9 and to a lesser extent by CYP2C19.

Phenytoin is a potent inducer of hepatic drug-metabolizing enzymes [see Drug Interactions (7.1, 7.2)].

12.5 Pharmacogenomics

CYP2C9 activity is decreased in individuals with genetic variants such as the CYP2C9*2 and CYP2C9*3 alleles. Carriers of variant alleles, resulting in intermediate (e.g., *1/*3, *2/*2) or poor metabolism (e.g., *2/*3, *3/*3) have decreased clearance of phenytoin. Other decreased or nonfunctional CYP2C9 alleles may also result in decreased clearance of phenytoin (e.g., *5, *6, *8, *11).

The prevalence of the CYP2C9 poor metabolizer phenotype is approximately 2-3% in the White population, 0.5-4% in the Asian population, and <1% in the African American population. The CYP2C9 intermediate phenotype prevalence is approximately 35% in the White population, 24% in the African American population, and 15-36% in the Asian population [see Warnings and Precautions (5.3) and Use in Specific Populations (8.7)].

13 NONCLINICAL TOXICOLOGY

13.1 Carcinogenesis, Mutagenesis, Impairment of Fertility

Carcinogenesis

[see Warnings and Precautions (5.9)]

In carcinogenicity studies, phenytoin was administered in the diet to mice (10, 25, or 45 mg/kg/day) and rats (25, 50, or 100 mg/kg/day) for 2 years. The incidences of hepatocellular tumors were increased in male and female mice at the highest dose. No increases in tumor incidence were observed in rats. The highest doses tested in these studies were associated with peak serum phenytoin levels below human therapeutic concentrations.

In carcinogenicity studies reported in the literature, phenytoin was administered in the diet for 2 years at doses up to 600 ppm (approximately 160 mg/kg/day) to mice and up to 2400 ppm (approximately 120 mg/kg/day) to rats. The incidences of hepatocellular tumors were increased in female mice at all but the lowest dose tested. No increases in tumor incidence were observed in rats.

Mutagenesis

Phenytoin was negative in the Ames test and in the in vitro clastogenicity assay in Chinese hamster ovary (CHO) cells.

In studies reported in the literature, phenytoin was negative in the in vitro mouse lymphoma assay and the in vivo micronucleus assay in mouse. Phenytoin was clastogenic in the in vitro sister chromatid exchange assay in CHO cells.

Fertility

Phenytoin has not been adequately assessed for effects on male or female fertility.

16 HOW SUPPLIED/STORAGE AND HANDLING

16.1 How Supplied

DILANTIN-125 Oral Suspension is supplied as follows:

Package Configuration | Strength | NDC
8 oz amber polyethylene terephthalate (PET) bottles | 125 mg phenytoin/5 mL | 58151-115-35

DILANTIN-125 Suspension (phenytoin oral suspension, USP), 125 mg phenytoin/5 mL contains a maximum alcohol content not greater than 0.6 percent in an orange suspension with an orange-vanilla flavor.

16.2 Storage and Handling

Store at 20° to 25°C (68° to 77°F); see USP controlled room temperature.

Protect from light. Do not freeze.

17 PATIENT COUNSELING INFORMATION

Advise patients to read the FDA-approved patient labeling (Medication Guide).

Administration Information

Advise patients taking phenytoin of the importance of adhering strictly to the prescribed dosage regimen, and of informing the physician of any clinical condition in which it is not possible to take the drug orally as prescribed, e.g., surgery, etc.

Instruct patients to use an accurately calibrated measuring device when using this medication to ensure accurate dosing.

Withdrawal of Antiepileptic Drugs

Advise patients not to discontinue use of DILANTIN without consulting with their healthcare provider. DILANTIN should normally be gradually withdrawn to reduce the potential for increased seizure frequency and status epilepticus [see Warnings and Precautions (5.1)].

Suicidal Ideation and Behavior

Counsel patients, their caregivers, and families that AEDs, including DILANTIN, may increase the risk of suicidal thoughts and behavior and advise them of the need to be alert for the emergence or worsening of symptoms of depression, any unusual changes in mood or behavior, or the emergence of suicidal thoughts, behavior, or thoughts about self-harm. Behaviors of concern should be reported immediately to healthcare providers [see Warnings and Precautions (5.2)].

Serious Dermatologic Reactions

Advise patients of the early signs and symptoms of severe cutaneous adverse reactions and to report any occurrence immediately to a physician [see Warnings and Precautions (5.3)].

Potential Signs of Drug Reaction with Eosinophilia and Systemic Symptoms (DRESS) and Other Systemic Reactions

Advise patients of the early toxic signs and symptoms of potential hematologic, dermatologic, hypersensitivity, or hepatic reactions. These symptoms may include, but are not limited to, fever, sore throat, rash, ulcers in the mouth, easy bruising, lymphadenopathy, facial swelling, and petechial or purpuric hemorrhage, and in the case of liver reactions, anorexia, nausea/vomiting, or jaundice. Advise the patient that, because these signs and symptoms may signal a serious reaction, that they must report any occurrence immediately to a physician. In addition, advise the patient that these signs and symptoms should be reported even if mild or when occurring after extended use [see Warnings and Precautions (5.3, 5.4, 5.5, 5.8, 5.9)].

Cardiac Effects

Counsel patients that cases of bradycardia and cardiac arrest have been reported, both at recommended phenytoin doses and levels, and in association with phenytoin toxicity. Patients should report cardiac signs or symptoms to their healthcare provider [see Warnings and Precautions (5.6) and Overdosage (10)].

Angioedema

Advise patients to discontinue DILANTIN and seek immediate medical care if they develop signs or symptoms of angioedema, such as facial, perioral, or upper airway swelling [see Warnings and Precautions (5.7)].

Effects of Alcohol Use and Other Drugs and Over-the-Counter Drug Interactions

Caution patients against the use of other drugs or alcoholic beverages without first seeking their physician’s advice [see Drug Interactions (7.1, 7.2)].

Inform patients that certain over-the-counter medications (e.g., antacids, cimetidine, and omeprazole), vitamins (e.g., folic acid), and herbal supplements (e.g., St. John’s wort) can alter their phenytoin levels.

Hyperglycemia

Advise patients that DILANTIN may cause an increase in blood glucose levels [see Warnings and Precautions (5.14)].

Gingival Hyperplasia

Advise patients of the importance of good dental hygiene in order to minimize the development of gingival hyperplasia and its complications.

Neurologic Effects

Counsel patients that DILANTIN may cause dizziness, gait disturbance, decreased coordination and somnolence. Advise patients taking DILANTIN not to drive, operate complex machinery, or engage in other hazardous activities until they have become accustomed to any such effects associated with DILANTIN.

Use in Pregnancy

Inform pregnant women and women of childbearing potential that use of DILANTIN during pregnancy can cause fetal harm, including an increased risk for cleft lip and/or cleft palate (oral clefts), cardiac defects, dysmorphic skull and facial features, nail and digit hypoplasia, growth abnormalities (including microcephaly), and cognitive deficits. When appropriate, counsel pregnant women and women of childbearing potential about alternative therapeutic options. Advise women of childbearing potential who are not planning a pregnancy to use effective contraception while using DILANTIN, keeping in mind that there is a potential for decreased hormonal contraceptive efficacy [see Drug Interactions (7.2)].

Instruct patients to notify their physician if they become pregnant or intend to become pregnant during therapy, and to notify their physician if they are breastfeeding or intend to breastfeed during therapy [see Use in Specific Populations (8.1, 8.2)].

Encourage patients to enroll in the North American Antiepileptic Drug (NAAED) Pregnancy Registry if they become pregnant. This registry is collecting information about the safety of antiepileptic drugs during pregnancy [see Use in Specific Populations (8.1)].

Distributed by:
Viatris Specialty LLC
Morgantown, WV 26505 U.S.A.

© 2023 Viatris Inc.

DILANTIN-125 is a registered trademark of Viatris Specialty LLC, a Viatris Company.

UPJ:DLNTNOS:R1

Revised: 2/2023

Medication Guide

DILANTIN-125® (Dī LAN' tĭn-125) (phenytoin) oral suspension

What is the most important information I should know about DILANTIN?

1. Do not stop taking DILANTIN without first talking to your healthcare provider.
  1. Stopping DILANTIN suddenly can cause serious problems.
  2. Stopping a seizure medicine suddenly can cause you to have seizures more often or seizures that will not stop (status epilepticus).
2. Like other antiepileptic drugs, DILANTIN may cause suicidal thoughts or actions in a very small number of people, about 1 in 500. Call a healthcare provider right away if you have any of these symptoms, especially if they are new, worse, or worry you:

- Thoughts about suicide or dying
- Attempts to commit suicide
- New or worse depression

- New or worse anxiety
- Feeling agitated or restless
- Panic attacks

- Trouble sleeping (insomnia)
- New or worse irritability
- Acting aggressive, being angry, or violent

- Acting on dangerous impulses
- An extreme increase in activity and talking (mania)
- Other unusual changes in behavior or mood

Suicidal thoughts or actions can be caused by things other than medicines. If you have suicidal thoughts or actions, your healthcare provider may check for other causes.

How can I watch for early symptoms of suicidal thoughts and actions?

- Pay attention to any changes, especially sudden changes, in mood, behaviors, thoughts, or feelings.
- Keep all follow-up visits with your healthcare provider as scheduled.

Call your healthcare provider between visits as needed, especially if you are worried about symptoms.

3. DILANTIN can cause a type of serious allergic reaction that may affect different parts of the body such as your liver, kidneys, blood, heart, skin or other parts of your body. These can be very serious and cause death. Call your healthcare provider right away if you have any or all of these symptoms:

- Fever
- Rash
- Swollen lymph glands
- Swelling of your face, eye, lips, or tongue
- Trouble swallowing or breathing

- Sore throat
- Sores in your mouth
- Bruise easily
- Purple or red spots on your skin
- Increase infections

- Not wanting to eat (anorexia)
- Nausea
- Vomiting
- Yellowing of the skin and the white part of your eyes (jaundice)

Call your healthcare provider even if the symptoms are mild or if you have been taking DILANTIN for an extended period of time. These symptoms can be a sign of a serious allergic reaction.

4. DILANTIN can cause problems with your heart, including a slow heartbeat. Let your healthcare provider know right away if you have any of these symptoms:
2. dizziness
3. tiredness
4. feeling like your heart is beating slowly or skipping beats
5. chest pain

What is DILANTIN?

DILANTIN is a prescription medicine used to treat certain types of seizures called tonic-clonic (grand mal) and psychomotor (temporal lobe) seizures.

Do not take DILANTIN if you:

- Are allergic to phenytoin or any of the ingredients in DILANTIN. See the end of this leaflet for a complete list of ingredients in DILANTIN.
- Have had an allergic reaction to CEREBYX (fosphenytoin), PEGANONE (ethotoin), or MESANTOIN (mephenytoin).
- Have had liver problems from taking phenytoin.
- Take delavirdine.

Before taking DILANTIN, tell your healthcare provider about all of your medical conditions, including if you:

- Have or have had depression, mood problems, or suicidal thoughts or behavior
- Have had an allergic reaction to a medicine similar to DILANTIN called carboxamides, barbiturates, succinimides, and oxazolidinediones
- Have or had liver or kidney problems
- Have or had an enzyme problem called porphyria
- Have or had high blood sugar (hyperglycemia)
- Drink alcohol
- Are pregnant or plan to become pregnant. DILANTIN may harm your unborn baby.
  - If you take DILANTIN during pregnancy, your baby is at risk for serious birth defects.
  - If you become pregnant while taking DILANTIN, the level of DILANTIN in your blood may decrease, causing your seizures to become worse. Your healthcare provider may change your dose of DILANTIN.
  - If you take DILANTIN during pregnancy, your baby is also at risk for bleeding problems right after birth. Your healthcare provider may give you and your baby medicine to prevent this.
  - All women of child-bearing age should talk to their healthcare provider about using other possible treatments instead of DILANTIN.
  - If you are of childbearing age and are not planning on getting pregnant, you should use effective birth control (contraception) while taking DILANTIN.
  - Pregnancy Registry: If you become pregnant while taking DILANTIN, talk to your healthcare provider about registering with the North American Antiepileptic Drug Pregnancy Registry. You can enroll in this registry by calling 1-888-233-2334. The purpose of this registry is to collect information about the safety of antiepileptic drugs during pregnancy.
- Are breastfeeding or plan to breastfeed. DILANTIN can pass into breast milk. You and your healthcare provider should decide if you will take DILANTIN while you are breastfeeding.

Tell your healthcare provider about all the medicines you take, including prescription and over-the-counter medicines, vitamins, and herbal supplements. These medicines can change the levels of DILANTIN in your blood.

Taking DILANTIN with certain other medicines can cause side effects or affect how well they work. Do not start or stop other medicines without talking to your healthcare provider.

Know the medicines you take. Keep a list of them and show it to your healthcare provider and pharmacist when you get a new medicine.

How should I take DILANTIN?

- Take DILANTIN exactly as your healthcare provider tells you.
- Your healthcare provider will tell you how much DILANTIN to take and when to take it.
- Your healthcare provider may change your dose if needed. Do not change your dose of DILANTIN without talking to your healthcare provider.
- If your healthcare provider has prescribed DILANTIN oral suspension, ask your pharmacist for a medicine dropper or medicine cup to help you measure the correct amount of DILANTIN. Do not use a household teaspoon. Ask your pharmacist for instructions on how to use the measuring device the right way.
- Do not stop taking DILANTIN without first talking to your healthcare provider. Stopping DILANTIN suddenly can cause serious problems.

What should I avoid while taking DILANTIN?

- Do not drink alcohol while you take DILANTIN without first talking to your healthcare provider. Drinking alcohol while taking DILANTIN may change your blood levels of DILANTIN which can cause serious problems.
- Do not drive, operate heavy machinery, or do other dangerous activities until you know how DILANTIN affects you. DILANTIN can slow your thinking and motor skills.

What are the possible side effects of DILANTIN?

See “What is the most important information I should know about DILANTIN?”

DILANTIN may cause other serious side effects including:

- Liver problems.
- Low blood count which could increase your chance of getting infections, bruising, bleeding and increased fatigue.
- Softening of your bones (osteopenia, osteoporosis, and osteomalacia) can cause your bones to break (fractures).
- High blood sugar (hyperglycemia).
- High levels of DILANTIN in your blood that could cause confusion also known as delirium, psychosis or a more serious condition that affects how your brain works (encephalopathy).

Call your healthcare provider right away, if you have any of the symptoms listed above.

The most common side effects of DILANTIN include:

- Irregular movement of the eye (nystagmus)
- Problems with movement and balance (ataxia)

- Slurred speech
- Decrease in coordination

- Drowsiness (somnolence)
- Confusion

DILANTIN can cause overgrowth of your gums. Brushing and flossing your teeth and seeing a dentist regularly while taking DILANTIN can help prevent this from happening.

These are not all of the possible side effects of DILANTIN.

Call your doctor for medical advice about side effects. You may report side effects to FDA at 1-800-FDA-1088.

How should I store DILANTIN?

- Store DILANTIN Suspension at room temperature between 68°F to 77°F (20°C to 25°C).
- Protect from light.
- Do not freeze.

Keep DILANTIN and all medicines out of the reach of children.

General information about the safe and effective use of DILANTIN.

Medicines are sometimes prescribed for purposes other than those listed in a Medication Guide. Do not use DILANTIN for a condition for which it was not prescribed. Do not give DILANTIN to other people, even if they have the same symptoms that you have. It may harm them. You can ask your pharmacist or healthcare provider for information about DILANTIN that is written for health professionals.

What are the ingredients in DILANTIN Suspension?

Active ingredient: phenytoin, USP

Inactive ingredients: alcohol, USP (maximum content not greater than 0.6 percent); banana flavor; carboxymethylcellulose sodium, USP; citric acid, anhydrous, USP; glycerin, USP; magnesium aluminum silicate, NF; orange oil concentrate; polysorbate 40, NF; purified water, USP; sodium benzoate, NF; sucrose, NF; vanillin, NF; and FD&C yellow No. 6.

Distributed by:
Viatris Specialty LLC
Morgantown, WV 26505 U.S.A.

© 2023 Viatris Inc.

DILANTIN-125 is a registered trademark of Viatris Specialty LLC, a Viatris Company.

The brands listed are trademarks of their respective owners.

For more information about DILANTIN, call Viatris at 1-877-446-3679 (1-877-4-INFO-RX).

This Medication Guide has been approved by the U.S. Food and Drug Administration Revised: 2/2023

UPJ:MG:DLNTNOS:R1

PRINCIPAL DISPLAY PANEL - 125 mg phenytoin/5 mL

ALWAYS DISPENSE WITH MEDICATION GUIDE

NDC 58151-115-35

Dilantin-125®
(phenytoin, USP)
Oral Suspension

125 mg per 5 mL

IMPORTANT–SHAKE WELL
BEFORE EACH USE
NOT FOR PARENTERAL USE

8 fl oz (237 mL)

Rx only

THIS PRODUCT MUST BE SHAKEN WELL
ESPECIALLY PRIOR TO INITIAL USE.

Each 5 mL contains 125 mg phenytoin,
with a maximum alcohol content not
greater than 0.6 percent.

DOSAGE AND USE
Adults, 1 teaspoonful (5 mL) three times
daily; pediatric patients, see package
insert.

Advice to Pharmacist and Patient–A
calibrated measuring device is
recommended to measure and deliver the
prescribed dose accurately. A household
teaspoon or tablespoon is not an
adequate measuring device.

See package insert for complete
prescribing information.

Store at 20° to 25°C (68° to 77°F); see
USP controlled room temperature.
Protect from light. Do not freeze.
Keep this and all drugs out of the
reach of children.

Distributed by:
Viatris Specialty LLC
Morgantown, WV 26505 U.S.A.

© 2023 Viatris Inc.

DILANTIN-125 is a registered trademark of Viatris
Specialty LLC, a Viatris Company.

UPJ:115:1C:R1